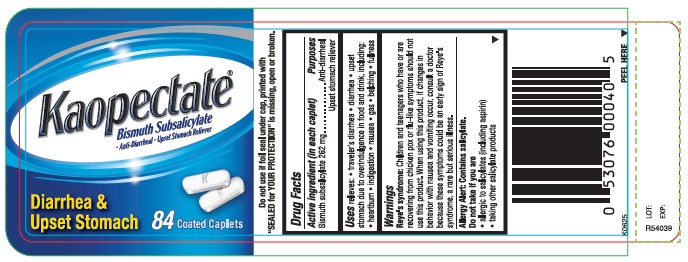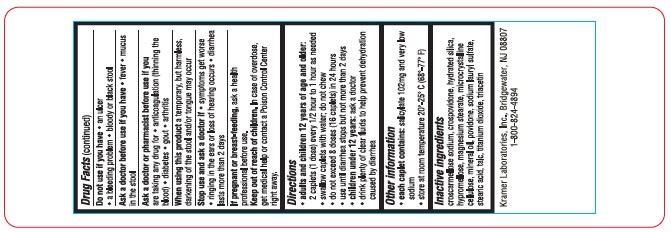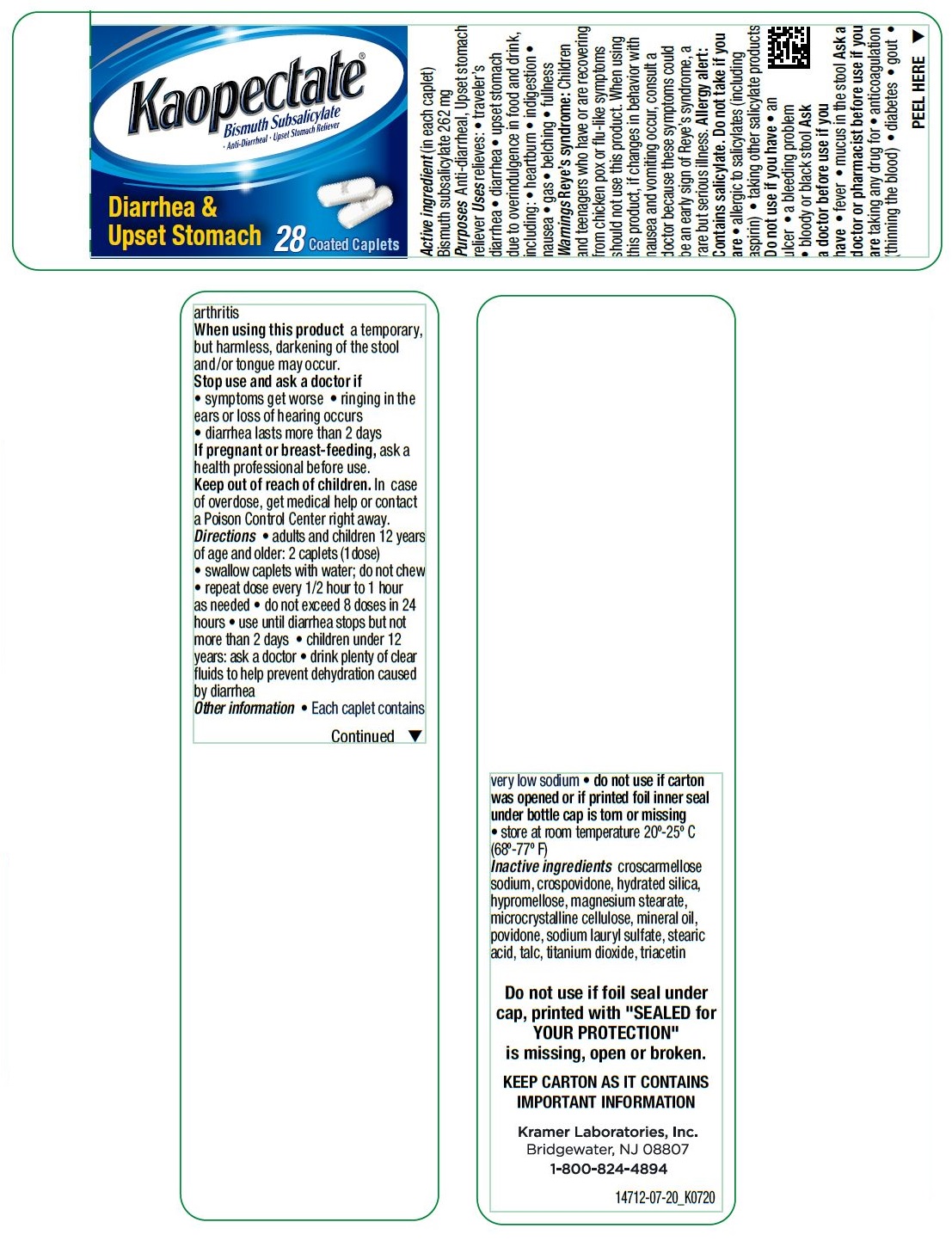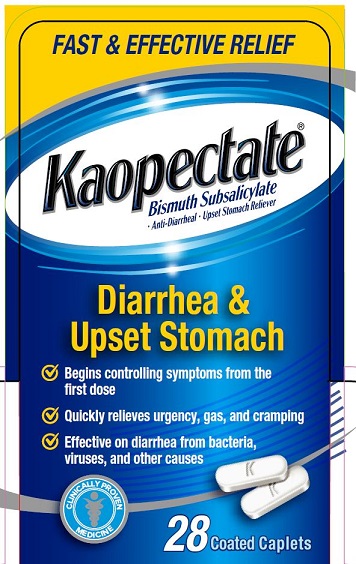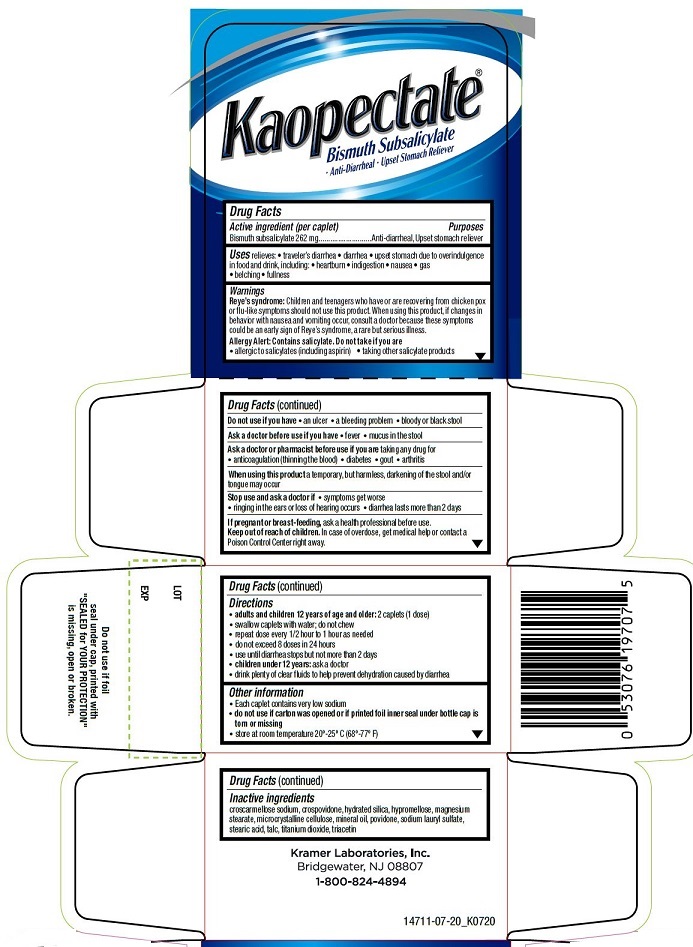 DRUG LABEL: Kaopectate
NDC: 55505-197 | Form: TABLET, COATED
Manufacturer: Kramer Laboratories
Category: otc | Type: HUMAN OTC DRUG LABEL
Date: 20251219

ACTIVE INGREDIENTS: Bismuth Subsalicylate 262 mg/1 1
INACTIVE INGREDIENTS: Croscarmellose Sodium; Crospovidone; Hydrated Silica; Hypromellose, Unspecified; Magnesium Stearate; Microcrystalline Cellulose; Mineral Oil; Povidone, Unspecified; Sodium Lauryl Sulfate; Stearic Acid; Talc; Titanium Dioxide; Triacetin

Drug Facts

ACTIVE INGREDIENT

Active ingredient (per caplet) | Purposes
Bismuth subsalicylate 262 mg | Anti-diarrheal, Upset stomach reliever

INDICATIONS AND USAGE

Uses relieves:

- traveler’s diarrhea
- diarrhea
- upset stomach due to overindulgence in food and drink, including:
  - heartburn
  - indigestion
  - nausea
  - gas
  - belching
  - fullness

Warnings

Reye’s syndrome: Children and teenagers who have or are recovering from chicken pox or flu-like symptoms should not use this product. When using this product, if changes in behavior with nausea and vomiting occur, consult a doctor because these symptoms could be an early sign of Reye’s syndrome, a rare but serious illness.

Allergy Alert: Contains salicylate.

Do not take if you are

- allergic to salicylates (including aspirin)
- taking other salicylate products

Do not use if you have

- an ulcer
- a bleeding problem
- bloody or black stool

Ask a doctor before use if you have

- fever
- mucus in the stool

Ask a doctor or pharmacist before use if you are taking any drug for

- anticoagulation (thinning the blood)
- diabetes
- gout
- arthritis

When using this product a temporary, but harmless, darkening of the stool and/or tongue may occur

Stop use and ask a doctor if

- symptoms get worse
- ringing in the ears or loss of hearing occurs
- diarrhea lasts more than 2 days

PREGNANCY OR BREAST FEEDING

If pregnant or breast-feeding, ask a health professional before use.

Keep out of reach of children. In case of overdose, get medical help or contact a Poison Control Center right away.

Directions

- adults and children 12 years of age and older: 2 caplets (1 dose)
- swallow caplets with water; do not chew
- repeat dose every 1/2 hour to 1 hour as needed
- do not exceed 8 doses in 24 hours
- use until diarrhea stops but not more than 2 days
- children under 12 years: ask a doctor
- drink plenty of clear fluids to help prevent dehydration caused by diarrhea

Other information

- Each caplet contains very low sodium
- do not use if carton was opened or if printed foil inner seal under bottle cap is torn or missing
- store at room temperature 20º-25º C (68º-77º F)

Inactive ingredients

croscarmellose sodium, crospovidone, hydrated silica, hypromellose, magnesium stearate, microcrystalline cellulose, mineral oil, povidone, sodium lauryl sulfate, stearic acid, talc, titanium dioxide, triacetin

Principal Display Panel

FAST & EFFECTIVE RELIEF
Kaopectate®
Bismuth Subsalicylate
• Anti-Diarrheal • Upset Stomach Reliver
Diarrhea &
Upset Stomach
✓ Begins controlling symptoms from the first dose
✓ Quickly relieves urgency, gas, and cramping
✓ Effective on diarrhea from bacteria, viruses, and other causes
CLINICALLY PROVEN MEDICINE
28 Coated Caplets

LOT
EXP
Do not use if foil seal under cap, printed with "SEALED for YOUR PROTECTION" is missing, open or broken.
Kramer Laboratories, Inc.
Bridgewater, NJ 08807
1-800-824-4894
14711-07-20_K0720

Kaopectate®
Bismuth Subsalicylate

- Anti-Diarrheal
- Upset Stomach Reliever

Diarrhea & Upset Stomach
28 Coated Caplets
Do not use if foil seal under cap, printed with "SEALED for YOUR PROTECTION" is missing, open or broken.
KEEP CARTON AS IT CONTAINS IMPORTANT INFORMATION
Kramer Laboratories, Inc.
Bridgewater, NJ 08807
1-800-824-4894
14712-07-20_K0720

Kaopectate®
Bismuth Subsalicylate

- Anti-Diarrheal
- Upset Stomach Reliever

Diarrhea & Upset Stomach
84 Coated Caplets
Do not use if foil seal under cap, printed with "SEALED for YOUR PROTECTION" is missing, open or broken.
K0625
LOT:
EXP:
R54039
Kramer Laboratories, Inc. Bridgewater, NJ 08807
1-800-824-4894